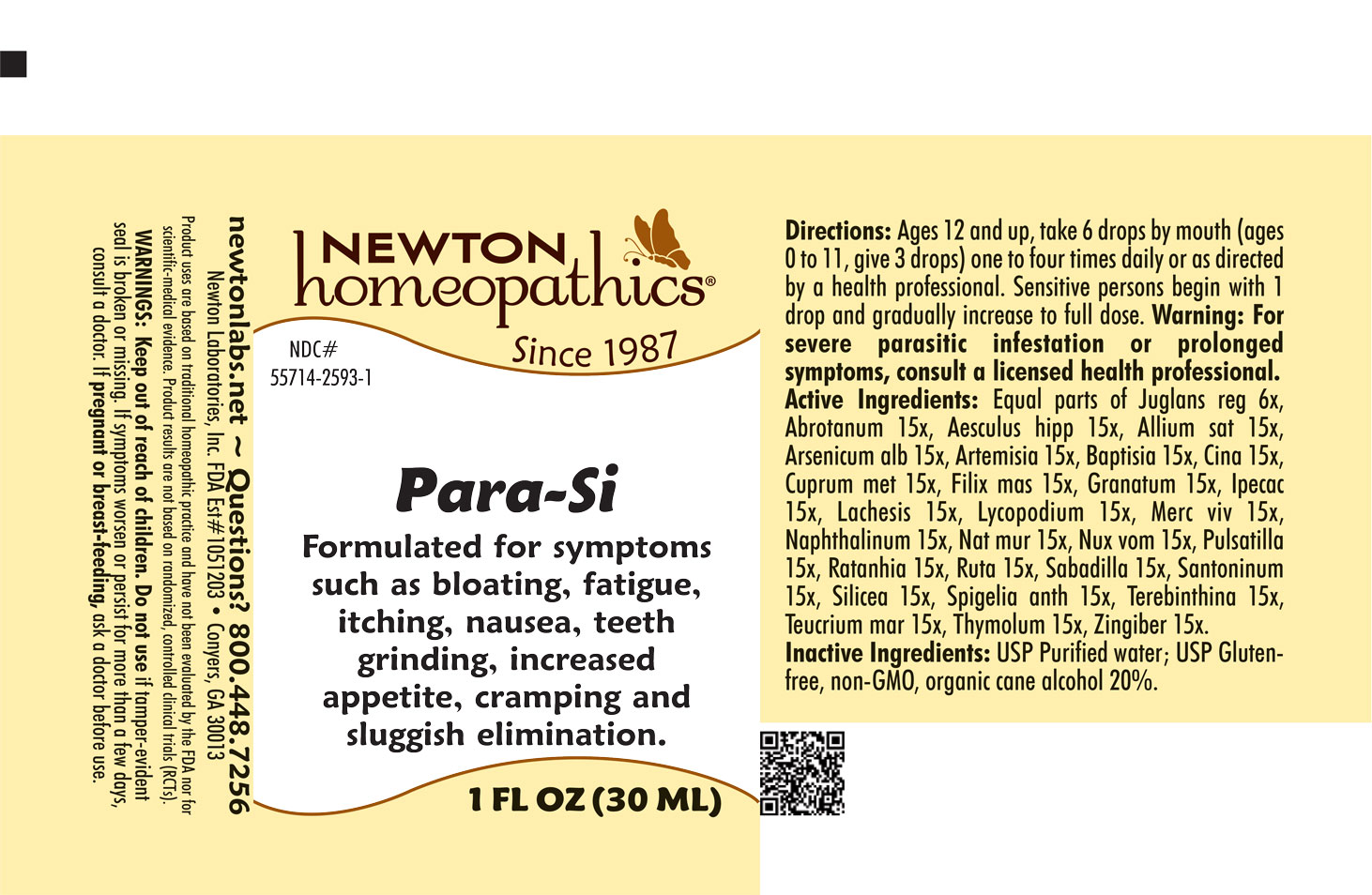 DRUG LABEL: Para-Si
NDC: 55714-2593 | Form: LIQUID
Manufacturer: Newton Laboratories, Inc.
Category: homeopathic | Type: HUMAN OTC DRUG LABEL
Date: 20241126

ACTIVE INGREDIENTS: TEUCRIUM MARUM 15 [hp_X]/1 mL; ARTEMISIA VULGARIS ROOT 15 [hp_X]/1 mL; DRYOPTERIS FILIX-MAS ROOT 15 [hp_X]/1 mL; JUGLANS REGIA LEAF 6 [hp_X]/1 mL; SPIGELIA ANTHELMIA 15 [hp_X]/1 mL; THYMOL 15 [hp_X]/1 mL; GARLIC 15 [hp_X]/1 mL; ARSENIC TRIOXIDE 15 [hp_X]/1 mL; BAPTISIA TINCTORIA ROOT 15 [hp_X]/1 mL; ARTEMISIA CINA PRE-FLOWERING TOP 15 [hp_X]/1 mL; COPPER 15 [hp_X]/1 mL; PUNICA GRANATUM ROOT BARK 15 [hp_X]/1 mL; IPECAC 15 [hp_X]/1 mL; LACHESIS MUTA VENOM 15 [hp_X]/1 mL; LYCOPODIUM CLAVATUM SPORE 15 [hp_X]/1 mL; MERCURY 15 [hp_X]/1 mL; ARTEMISIA ABROTANUM FLOWERING TOP 15 [hp_X]/1 mL; NAPHTHALENE 15 [hp_X]/1 mL; SODIUM CHLORIDE 15 [hp_X]/1 mL; STRYCHNOS NUX-VOMICA SEED 15 [hp_X]/1 mL; ANEMONE PULSATILLA 15 [hp_X]/1 mL; KRAMERIA LAPPACEA ROOT 15 [hp_X]/1 mL; RUTA GRAVEOLENS FLOWERING TOP 15 [hp_X]/1 mL; SCHOENOCAULON OFFICINALE SEED 15 [hp_X]/1 mL; SANTONIN 15 [hp_X]/1 mL; HORSE CHESTNUT 15 [hp_X]/1 mL; GINGER 15 [hp_X]/1 mL; SILICON DIOXIDE 15 [hp_X]/1 mL; TURPENTINE OIL 15 [hp_X]/1 mL
INACTIVE INGREDIENTS: ALCOHOL; WATER

Para-Si 2593L

INDICATIONS & USAGE SECTION

Formulated for symptoms such as bloating, fatigue, itching, nausea, teeth grinding, increased appetite, cramping, sluggish elimination and other related symptoms.

DOSAGE & ADMINISTRATION SECTION

Directions: Ages 12 and up, take 6 drops by mouth (ages 0 to 11, give 3 drops) one to four times daily or as directed by a health professional. Sensitive persons begin with 1 drop and gradually increase to full dose. Warning: For severe parasitic infestation or prolonged symptoms, consult a licensed health professional.

OTC - ACTIVE INGREDIENT SECTION

Equal parts of Juglans reg 6x, Abrotanum 15x, Aesculus hipp 15x, Allium sat 15x, Arsenicum alb 15x, Artemisia 15x, Baptisia 15x, Cina 15x, Cuprum met 15x, Filix mas 15x, Granatum 15x, Ipecac 15x, Lachesis 15x, Lycopodium 15x, Mercurius viv 15x, Naphthalinum 15x, Nat mur 15x, Nux vom 15x, Pulsatilla 15x, Ratanhia 15x, Ruta 15x, Sabadilla 15x, Santoninum 15x, Silicea 15x, Spigelia anth 15x, Terebinthina 15x, Teucrium mar 15x, Thymolum 15x, Zingiber 15x.

OTC - PURPOSE SECTION

Formulated for symptoms such as bloating, fatigue, itching, nausea, teeth grinding, increased appetite, cramping and sluggish elimination.

WARNINGS SECTION

WARNINGS: Keep out of reach of children. Do not use if tamper-evident seal is broken or missing. If symptoms worsen or persist for more than a few days, consult a doctor. If pregnant or breast-feeding, ask a doctor before use.

OTC - PREGNANCY OR BREAST FEEDING SECTION

If pregnant or breast-feeding, ask a doctor before use.

OTC - KEEP OUT OF REACH OF CHILDREN SECTION

Keep out of reach of children.

INACTIVE INGREDIENT SECTION

Inactive Ingredients: USP Purified Water; USP Gluten-free, non-GMO, organic cane alcohol 20%.

QUESTIONS SECTION

newtonlabs.net – Questions? 800.448.7256

Newton Laboratories, Inc. FDA Est # 1051203 - Conyers, GA 30013